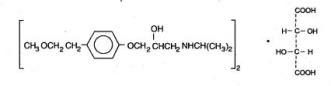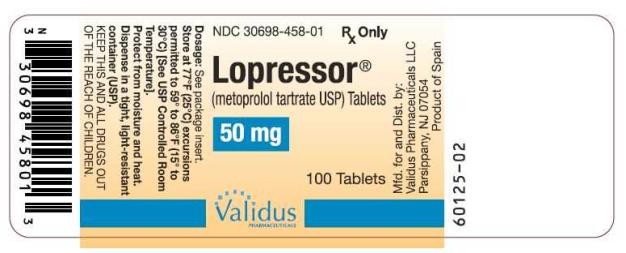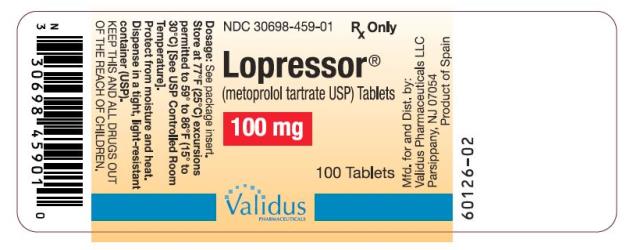 DRUG LABEL: Lopressor
NDC: 30698-458 | Form: TABLET
Manufacturer: Validus Pharmaceuticals LLC
Category: prescription | Type: HUMAN PRESCRIPTION DRUG LABEL
Date: 20230914

ACTIVE INGREDIENTS: METOPROLOL TARTRATE 50 mg/1 1
INACTIVE INGREDIENTS: CELLULOSE, MICROCRYSTALLINE; SILICON DIOXIDE; D&C RED NO. 30; LACTOSE, UNSPECIFIED FORM; MAGNESIUM STEARATE; POLYETHYLENE GLYCOL, UNSPECIFIED; PROPYLENE GLYCOL; POVIDONE; SODIUM STARCH GLYCOLATE TYPE A POTATO; TALC; TITANIUM DIOXIDE

HIGHLIGHTS OF PRESCRIBING INFORMATION

These highlights do not include all the information needed to use LOPRESSOR safely and effectively. See full prescribing information for LOPRESSOR.
LOPRESSOR (metoprolol tartrate) tablets, for oral use
Initial U.S. Approval: 1992

1 INDICATIONS AND USAGE

LOPRESSOR is a beta-adrenergic blocker indicated for the treatment of:

- Hypertension, to lower blood pressure. Lowering blood pressure reduces the risk of fatal and non-fatal cardiovascular events, primarily strokes and myocardial infarctions. (1.1)
- Angina Pectoris. (1.2)
- Myocardial Infarction, to reduce the risk of cardiovascular mortality when used in conjunction with intravenous metoprolol therapy in patients with definite or suspected acute myocardial infarction in hemodynamically stable patients. (1.3)

2 DOSAGE AND ADMINISTRATION

- Administer once daily with food or after a meal. Titrate at weekly or longer intervals as needed and tolerated. (2)
- Hypertension: Recommended starting dosage is 100 mg daily, in single or divided doses. (2.1)
- Angina Pectoris: Recommended starting dosage is 100 mg daily, given as two divided doses. (2.2)
- Myocardial Infarction: The starting dosage depends upon tolerance of intravenous metoprolol, see full prescribing information. (2.3)

3 DOSAGE FORMS AND STRENGTHS

- LOPRESSOR (metoprolol tartrate) tablets: 50 mg and 100 mg. (3)

4 CONTRAINDICATIONS

- Known hypersensitivity to product components. (4)
- Severe bradycardia: Greater than first degree heart block, or sick sinus syndrome without a pacemaker. (4)
- Cardiogenic shock or decompensated heart failure. (4)

5 WARNINGS AND PRECAUTIONS

- Abrupt cessation may exacerbate myocardial ischemia. (5.1)
- Heart Failure: Worsening cardiac failure may occur. (5.2)
- Bronchospastic Disease: Avoid beta-blockers. (5.3)
- Pheochromocytoma: Initiate therapy with an alpha blocker. (5.4)
- Major Surgery: Avoid initiation of high-dose extended-release metoprolol in patients undergoing non-cardiac surgery. Do not routinely withdraw chronic beta-blocker therapy prior to surgery. (5.5, 6.1)
- Diabetes: May mask symptoms of hypoglycemia. (5.6)
- Thyrotoxicosis: Abrupt withdrawal in patients with thyrotoxicosis might precipitate a thyroid storm. (5.7)
- Peripheral Vascular Disease: Can aggravate symptoms of arterial insufficiency. (5.9)

6 ADVERSE REACTIONS

- Most common adverse reactions: tiredness, dizziness, depression, shortness of breath, bradycardia, hypotension, diarrhea, pruritus, rash. (6.1)

To report SUSPECTED ADVERSE REACTIONS, contact Validus Pharmaceuticals LLC at 1-866-982-5438 or FDA at 1-800-FDA-1088 or www.fda.gov/medwatch.

7 DRUG INTERACTIONS

- Catecholamine-depleting drugs may have an additive effect when given with beta-blocking agents. (7.1)
- Patients may be unresponsive to the usual doses of epinephrine used to treat allergic reaction. (7.2)
- CYP2D6 Inhibitors are likely to increase metoprolol concentration. (7.3)
- Concomitant use of glycosides, clonidine, and diltiazem and verapamil with beta-blockers can increase the risk of bradycardia. (7.4)
- Beta-blockers including metoprolol, may exacerbate the rebound hypertension that can follow the withdrawal of clonidine. (7.4)

8 USE IN SPECIFIC POPULATIONS

- Hepatic Impairment: Consider initiating LOPRESSOR therapy at low doses and gradually increase dosage to optimize therapy, while monitoring closely for adverse events. (8.6)

FULL PRESCRIBING INFORMATION

1 INDICATIONS AND USAGE

1.1 Hypertension

LOPRESSOR is indicated for the treatment of hypertension in adult patients, to lower blood pressure. Lowering blood pressure lowers the risk of fatal and non-fatal cardiovascular events, primarily strokes and myocardial infarctions. These benefits have been seen in controlled trials of antihypertensive drugs from a wide variety of pharmacologic classes including metoprolol.

Control of high blood pressure should be part of comprehensive cardiovascular risk management, including, as appropriate, lipid control, diabetes management, antithrombotic therapy, smoking cessation, exercise, and limited sodium intake. Many patients will require more than 1 drug to achieve blood pressure goals. For specific advice on goals and management, see published guidelines, such as those of the National High Blood Pressure Education Program’s Joint National Committee on Prevention, Detection, Evaluation, and Treatment of High Blood Pressure (JNC).

Numerous antihypertensive drugs, from a variety of pharmacologic classes and with different mechanisms of action, have been shown in randomized controlled trials to reduce cardiovascular morbidity and mortality, and it can be concluded that it is blood pressure reduction, and not some other pharmacologic property of the drugs, that is largely responsible for those benefits. The largest and most consistent cardiovascular outcome benefit has been a reduction in the risk of stroke, but reductions in myocardial infarction and cardiovascular mortality also have been seen regularly.

Elevated systolic or diastolic pressure causes increased cardiovascular risk, and the absolute risk increase per mmHg is greater at higher blood pressures, so that even modest reductions of severe hypertension can provide substantial benefit. Relative risk reduction from blood pressure reduction is similar across populations with varying absolute risk, so the absolute benefit is greater in patients who are at higher risk independent of their hypertension (for example, patients with diabetes or hyperlipidemia), and such patients would be expected to benefit from more aggressive treatment to a lower blood pressure goal.

Some antihypertensive drugs have smaller blood pressure effects (as monotherapy) in black patients, and many antihypertensive drugs have additional approved indications and effects (e.g., on angina, heart failure, or diabetic kidney disease). These considerations may guide selection of therapy.

LOPRESSOR may be administered with other antihypertensive agents.

1.2 Angina Pectoris

LOPRESSOR is indicated in the long-term treatment of angina pectoris, to reduce angina attacks and to improve exercise tolerance.

1.3 Myocardial Infarction

Lopressor tablets are indicated in the treatment of hemodynamically stable patients with definite or suspected acute myocardial infarction to reduce cardiovascular mortality when used alone or in conjunction with intravenous metoprolol.

2 DOSAGE AND ADMINISTRATION

2.1 Hypertension

Individualize the dosage of Lopressor tablets. Lopressor tablets should be taken with or immediately following meals.

The usual initial dosage is 100 mg daily in single or divided doses. Adjust dosage at weekly (or longer) intervals until optimum blood pressure reduction is achieved. In general, the maximum effect of any given dosage level will be apparent after 1 week of therapy. The effective dosage range of Lopressor tablets is 100 mg to 450 mg per day. Dosages above 450 mg per day have not been studied. While once-daily dosing can maintain a reduction in blood pressure throughout the day, lower doses (especially 100 mg) may not maintain a full effect at the end of the 24-hour period. Larger or more frequent daily doses may be required. Measure blood pressure near the end of the dosing interval to determine whether satisfactory control is being maintained throughout the day.

2.2 Angina Pectoris

The dosage of Lopressor tablets should be individualized. Lopressor tablets should be taken with or immediately following meals.

The usual initial dosage is 100 mg daily, given in two divided doses. Gradually increase the dosage at weekly intervals until optimum clinical response has been obtained or there is a pronounced slowing of the heart rate. The effective dosage range of Lopressor tablets is 100 to 400 mg per day. Dosages above 400 mg per day have not been studied. If treatment is to be discontinued, reduce the dosage gradually over a period of 1 - 2 weeks [see Warnings and Precautions (5.1)].

2.3 Myocardial Infarction

See prescribing information of intravenous metoprolol for dosage instructions for intravenous therapy.

In patients who tolerate the full intravenous dose, initiate Lopressor tablets, 50 mg every 6 hours, 15 minutes after the last intravenous dose of metoprolol and continue for 48 hours. In the case of intolerance, reduce dose to 25 mg and administer for 48 hours. Titrate, based on tolerability, to a maintenance dosage of 100 mg twice daily. Continue therapy for at least 3 months. Although the efficacy of Lopressor beyond 3 months has not been conclusively established, data from studies with other beta-blockers suggest that treatment should be continued for 1 to 3 years.

3 DOSAGE FORMS AND STRENGTHS

LOPRESSOR is supplied as:

50 mg tablet – capsule shaped, biconvex, pink, scored (imprinted GEIGY on one side and 51 twice on the scored side)

100 mg tablet – capsule shaped, biconvex, light blue, scored (imprinted with GEIGY on one side and 71 twice on the scored side)

4 CONTRAINDICATIONS

LOPRESSOR is contraindicated in severe bradycardia, second- or third-degree heart block, cardiogenic shock, systolic blood pressure <100, decompensated heart failure, sick sinus syndrome (unless a permanent pacemaker is in place), and in patients who are hypersensitive to any component of this product.

5 WARNINGS AND PRECAUTIONS

5.1 Abrupt Cessation of Therapy

Following abrupt cessation of therapy with certain beta-blocking agents, exacerbations of angina pectoris and, in some cases, myocardial infarction have occurred. When discontinuing chronically administered LOPRESSOR, particularly in patients with ischemic heart disease, gradually reduce the dosage over a period of 1 to 2 weeks and monitor the patient. If angina markedly worsens or acute coronary ischemia develops, promptly reinstate LOPRESSOR, and take measures appropriate for the management of unstable angina. Warn patients not to interrupt therapy without their physician’s advice. Because coronary artery disease is common and may be unrecognized, avoid abruptly discontinuing LOPRESSOR in patients treated only for hypertension.

5.2 Heart Failure

Worsening cardiac failure may occur during up-titration of LOPRESSOR. If such symptoms occur, increase diuretics and restore clinical stability before advancing the dose of LOPRESSOR [see Dosage and Administration (2)]. It may be necessary to lower the dose of LOPRESSOR or temporarily discontinue it. Such episodes do not preclude subsequent successful titration of LOPRESSOR.

5.3 Bronchospastic Disease

Patients with bronchospastic disease, should in general, not receive beta-blockers, including Lopressor. Because of its relative beta1 cardio-selectivity, however, LOPRESSOR may be used in patients with bronchospastic disease who do not respond to, or cannot tolerate, other antihypertensive treatment. Because beta1-selectivity is not absolute, use the lowest possible dose of LOPRESSOR. Bronchodilators, including beta2-agonists, should be readily available or administered concomitantly [see Dosage and Administration (2)].

5.4 Pheochromocytoma

If LOPRESSOR is used in the setting of pheochromocytoma, it should be given in combination with an alpha blocker, and only after the alpha blocker has been initiated. Administration of beta-blockers alone in the setting of pheochromocytoma has been associated with a paradoxical increase in blood pressure due to the attenuation of beta-mediated vasodilatation in skeletal muscle.

5.5 Major Surgery

Avoid initiation of a high-dose regimen of beta-blocker therapy in patients undergoing non-cardiac surgery, since such use in patients with cardiovascular risk factors has been associated with bradycardia, hypotension, stroke and death.

Chronically administered beta-blocking therapy should not be routinely withdrawn prior to major surgery, however, the impaired ability of the heart to respond to reflex adrenergic stimuli may augment the risks of general anesthesia and surgical procedures.

5.6 Hypoglycemia

Beta-blockers may prevent early warning signs of hypoglycemia, such as tachycardia, and increase the risk for severe or prolonged hypoglycemia at any time during treatment, especially in patients with diabetes mellitus or children and patients who are fasting (i.e., surgery, not eating regularly, or are vomiting). If severe hypoglycemia occurs, patients should be instructed to seek emergency treatment. Beta-blockers may ask some of the manifestations of hypoglycemia, particularly tachycardia.

5.7 Thyrotoxicosis

Beta-adrenergic blockade may mask certain clinical signs of hyperthyroidism, such as tachycardia. Abrupt withdrawal of beta-blockade may precipitate a thyroid storm.

5.8 Risk of Anaphylactic Reactions

While taking beta-blockers, patients with a history of severe anaphylactic reaction to a variety of allergens may be more reactive to repeated challenge, either accidental, diagnostic, or therapeutic. Such patients may be unresponsive to the usual doses of epinephrine used to treat allergic reaction.

5.9 Peripheral Vascular Disease

Beta-blockers can precipitate or aggravate symptoms of arterial insufficiency in patients with peripheral vascular disease.

6 ADVERSE REACTIONS

The following adverse reactions are described elsewhere in labeling:

- Worsening angina or myocardial infarction [see Warnings and Precautions (5)]
- Worsening heart failure [see Warnings and Precautions (5)].
- Worsening AV block [see Contraindications (4)].

6.1 Clinical Trials Experience

Because clinical trials are conducted under widely varying conditions, adverse reaction rates observed in the clinical trials of a drug cannot be directly compared to rates in the clinical trials of another drug and may not reflect the rates observed in practice.

Hypertension and Angina

Most adverse effects have been mild and transient.

Central Nervous System: Tiredness and dizziness have occurred in about 10% of patients. Depression has been reported in about 5 of 100 patients. Mental confusion and short-term memory loss have been reported. Headache, nightmares, and insomnia have also been reported.

Cardiovascular: Shortness of breath and bradycardia have occurred in approximately 3% of patients. Cold extremities; arterial insufficiency, usually of the Raynaud type; palpitations; heart failure exacerbations; peripheral edema; and hypotension have been reported in about 1% of patients. Gangrene in patients with pre-existing severe peripheral circulatory disorders has also been reported. [see Contraindications (4) and Warnings and Precautions (5.2)].

Respiratory: Wheezing (bronchospasm) and dyspnea have been reported in about 1% of patients [see Warnings and Precautions (5.3)]. Rhinitis has also been reported.

Gastrointestinal: Diarrhea has occurred in about 5% of patients. Nausea, dry mouth, gastric pain, constipation, flatulence, and heartburn have been reported in about 1% of patients. Vomiting was a common occurrence.

Hypersensitive Reactions: Pruritus or rash have occurred in about 5% of patients. Photosensitivity and worsening of psoriasis has been reported.

Miscellaneous: Peyronie’s disease, musculoskeletal pain, blurred vision, and tinnitus has been reported.

Myocardial Infarction

In general, the adverse reactions observed in trials with metoprolol in MI are consistent with the hypertension and angina experience.

In a randomized comparison of Lopressor and placebo in the setting of acute MI the following adverse reactions were reported:

 | Lopressor® | Placebo
Hypotension (systolic BP < 90 mm Hg) | 27.4% | 23.2%
Bradycardia (heart rate < 40 beats/min) | 15.9% | 6.7%
Second- or third-degree heart block | 4.7% | 4.7%
First-degree heart block (P-R ≥ 0.26 sec) | 5.3% | 1.9%
Heart failure | 27.5% | 29.6%

6.2 Post-Marketing Experience

The following adverse reactions have been identified during post approval use of LOPRESSOR. Because these reactions are reported voluntarily from a population of uncertain size, it is not always possible to reliably estimate their frequency or establish a causal relationship to drug exposure.

Central Nervous System: Reversible mental depression progressing to catatonia; an acute reversible syndrome characterized by disorientation for time and place, short-term memory loss, emotional lability, slightly clouded sensorium, and decreased performance on neuropsychometrics.

Cardiovascular: Intensification of AV block [see Contraindications (4)].

Hematologic: Agranulocytosis, nonthrombocytopenic purpura and thrombocytopenic purpura.

Hypersensitive Reactions: Fever combined with aching and sore throat, laryngospasm and respiratory distress.

Laboratory Findings:

Increase in blood triglycerides, elevated transaminase and decrease in High Density Lipoprotein (HDL)

7 DRUG INTERACTIONS

7.1 Catecholamine Depleting Drugs

Catecholamine depleting drugs (e.g., reserpine, monoamine oxidase (MAO) inhibitors) may have an additive effect when given with beta-blocking agents. Observe patients treated with LOPRESSOR plus a catecholamine depletor for evidence of hypotension or marked bradycardia, which may produce vertigo, syncope, or postural hypotension.

7.2 Epinephrine

While taking beta-blockers, patients with a history of severe anaphylactic reactions to a variety of allergens may be more reactive to repeated challenge and may be unresponsive to the usual doses of epinephrine used to treat an allergic reaction.

7.3 CYP2D6 Inhibitors

Drugs that are strong inhibitors of CYP2D6 such as quinidine, fluoxetine, paroxetine, and propafenone were shown to double metoprolol concentrations. While there is no information about moderate or weak inhibitors, these too are likely to increase metoprolol concentration. Increases in plasma concentration decrease the cardioselectivity of metoprolol [see Clinical Pharmacology (12.3)]. Monitor patients closely, when the combination cannot be avoided.

7.4 Negative Chronotropes

Digitalis glycosides, clonidine, diltiazem and verapamil slow atrioventricular conduction and decrease heart rate. Concomitant use with beta-blockers can increase the risk of bradycardia.

If clonidine and a beta-blocker, such as metoprolol are coadministered, withdraw the beta-blocker several days before the gradual withdrawal of clonidine because beta-blockers may exacerbate the rebound hypertension that can follow the withdrawal of clonidine. If replacing clonidine by beta-blocker therapy, delay the introduction of beta-blockers for several days after clonidine administration has stopped.

8 USE IN SPECIFIC POPULATIONS

8.1 Pregnancy

Risk Summary

Available data from published observational studies have not demonstrated an association of adverse developmental outcomes with maternal use of metoprolol during pregnancy (see Data). Untreated hypertension and myocardial infarction during pregnancy can lead to adverse outcomes for the mother and the fetus (see Clinical Considerations). In animal reproduction studies, metoprolol has been shown to increase post-implantation loss and decrease neonatal survival in rats at oral dosages of 500 mg/kg/day, approximately 11 times the daily dose of 450 mg in a 60-kg patient on a mg/m^2 basis.

All pregnancies have a background risk of birth defect, loss, or other adverse outcomes. The estimated background risk of major birth defects and miscarriage for the indicated population is unknown. In the U.S. general population, the estimated background risk of major birth defects and miscarriage in clinically recognized pregnancies is 2 to 4% and 15 to 20%, respectively.

Clinical consideration

Disease-associated maternal and/or embryo/fetal risk

Hypertension in pregnancy increases the maternal risk for pre-eclampsia, gestational diabetes, premature delivery, and delivery complications (e.g., need for cesarean section, and post-partum hemorrhage). Hypertension increases the fetal risk for intrauterine growth restriction and intrauterine death. Pregnant women with hypertension should be carefully monitored and managed accordingly.

Fetal/Neonatal adverse reactions

Metoprolol crosses the placenta. Neonates born to mothers who are receiving metoprolol during pregnancy, may be at risk for hypotension, hypoglycemia, bradycardia, and respiratory depression. Observe neonates and manage accordingly.

Data

Human Data

Data from published observational studies did not demonstrate an association of major congenital malformations and use of metoprolol in pregnancy. The published literature has reported inconsistent findings of intrauterine growth retardation, preterm birth and perinatal mortality with maternal use of metoprolol during pregnancy; however, these studies have methodological limitations hindering interpretation. Methodological limitations include retrospective design, concomitant use of other medications, and other unadjusted confounders that may account for the study findings including the underlying disease in the mother. These observational studies cannot definitely establish or exclude any drug-associated risk during pregnancy.

Animal Data

Metoprolol has been shown to increase post-implantation loss and decrease neonatal survival in rats at oral dosages of 500 mg/kg/day, i.e., 11 times, on a mg/m^2 basis, the daily dose of 450 mg in a 60-kg patient.

No fetal abnormalities were observed when pregnant rats received metoprolol orally up to a dose of 200 mg/kg/day, i.e., 4 times, the daily dose of 400mg in a 60-kg patient.

8.2 Lactation

Risk Summary

Limited available data from published literature report that metoprolol is present in human milk. The estimated daily infant dose of metoprolol received from breastmilk ranges from 0.05 mg to less than 1 mg. The estimated relative infant dosage was 0.5% to 2% of the mother's weight-adjusted dosage (see Data). No adverse reactions of metoprolol on the breastfed infant have been identified. There is no information regarding the effects of metoprolol on milk production.

Clinical consideration

Monitoring for adverse reactions

For a lactating woman who is a slow metabolizer of metoprolol, monitor the breastfed infant for bradycardia and other symptoms of beta-blockade such as dry mouth, skin or eyes, diarrhea or constipation. In a report of 6 mothers taking metoprolol, none reported adverse effects in her breastfed infant.

Data

Limited published cases estimate the infant daily dose of metoprolol received from breast milk range from 0.05 mg to less than 1 mg.

In 2 women who were taking unspecified amount of metoprolol, milk samples were taken after one dose of metoprolol. The estimated amount of metoprolol and alpha-hydroxymetoprolol in breast milk is reported to be less than 2% of the mother's weight-adjusted dosage.

In a small study, breast milk was collected every 2 to 3 hours over one dosage interval, in three mothers (at least 3 months postpartum) who took metoprolol of unspecified amount. The average amount of metoprolol present in breast milk was 71.5 mcg/day (range 17.0 to 158.7). The average relative infant dosage was 0.5% of the mother's weight-adjusted dosage.

8.3 Females and Males of Reproductive Potential

Risk Summary

Based on the published literature, beta-blockers (including metoprolol) may cause erectile dysfunction and inhibit sperm motility. In animal fertility studies, metoprolol has been associated with reversible adverse effects on spermatogenesis starting at oral dose level of 3.5 mg/kg in rats, which would correspond to a dose of 34 mg/day in humans in mg/m^2 equivalent, although other studies have shown no effect of metoprolol on reproductive performance in male rats.

No evidence of impaired fertility due to metoprolol was observed in rats [see Nonclinical Toxicology (13.1)].

8.4 Pediatric Use

Safety and effectiveness of LOPRESSOR have not been established in pediatric patients.

8.5 Geriatric Use

Clinical studies of LOPRESSOR in hypertension did not include sufficient numbers of subjects aged 65 and over to determine whether they respond differently from younger subjects. Other reported clinical experience in hypertensive patients has not identified differences in responses between elderly and younger patients.

In worldwide clinical trials of Lopressor in myocardial infarction, where approximately 478 patients were over 65years of age (0 over 75 years of age), no age-related differences in safety and effectiveness were found. Other reported clinical experience in myocardial infarction has not identified differences in response between the elderly and younger patients.

In general, use a low initial starting dose in elderly patients given their greater frequency of decreased hepatic, renal, or cardiac function, and of concomitant disease or other drug therapy.

8.6 Hepatic Impairment

No studies have been performed with LOPRESSOR in patients with hepatic impairment. Because LOPRESSOR is metabolized by the liver, metoprolol blood levels are likely to increase substantially with poor hepatic function. Therefore, initiate therapy at doses lower than those recommended for a given indication; and increase doses gradually in patients with impaired hepatic function.

8.7 Renal Impairment

The systemic availability and half-life of metoprolol in patients with renal failure do not differ to a clinically significant degree from those in normal subjects. No reduction in dosage is needed in patients with chronic renal failure [see Clinical Pharmacology (12.3)].

10 OVERDOSAGE

Signs and Symptoms - Overdosage of LOPRESSOR may lead to severe bradycardia, hypotension, and cardiogenic shock. Clinical presentation can also include: atrioventricular block, heart failure, bronchospasm, hypoxia, impairment of consciousness/coma, nausea and vomiting.

Treatment – Consider treating the patient with intensive care. Patients with myocardial infarction or heart failure may be prone to significant hemodynamic instability. Beta-blocker overdose may result in significant resistance to resuscitation with adrenergic agents, including beta-agonists. On the basis of the pharmacologic actions of metoprolol, employ the following measures.

Hemodialysis is unlikely to make a useful contribution to metoprolol elimination [see Clinical Pharmacology (12.3)].

Bradycardia: Evaluate the need for atropine, adrenergic-stimulating drugs or pacemaker to treat bradycardia and conduction disorders.

Hypotension: Treat underlying bradycardia. Consider intravenous vasopressor infusion, such as dopamine or norepinephrine.

Heart failure and shock: May be treated when appropriate with suitable volume expansion, injection of glucagon (if necessary, followed by an intravenous infusion of glucagon), intravenous administration of adrenergic drugs such as dobutamine, with α1 receptor agonistic drugs added in presence of vasodilation.

Bronchospasm: Can usually be reversed by bronchodilators.

11 DESCRIPTION

Lopressor tablets contain metoprolol tartrate, a selective beta1-adrenoreceptor blocking agent. Metoprolol tartrate is (±)-1-(Isopropylamino)-3-[p-(2-methoxyethyl) phenoxy]-2-propanol L-(+)-tartrate (2:1) salt, and its structural formula is

Metoprolol tartrate USP is a white, practically odorless, crystalline powder with a molecular weight of 684.82. It is very soluble in water; freely soluble in methylene chloride, in chloroform, and in alcohol; slightly soluble in acetone; and insoluble in ether.

Lopressor is available as 50 mg and 100 mg tablets for oral administration containing 50 mg and 100 mg metoprolol tartrate, respectively.

Inactive Ingredients: Tablets contain microcrystalline cellulose, colloidal silicon dioxide, lactose monohydrate, magnesium stearate, povidone, sodium starch glycolate. Film coating contains Opadry YS-1-1419 Pink (50 mg tablets) or Opadry YS-1-4281 Blue (100 mg tablets).

12 CLINICAL PHARMACOLOGY

12.1 Mechanism of Action

Metoprolol is a beta1-selective (cardioselective) adrenergic receptor blocking agent. This preferential effect is not absolute, however, and at higher plasma concentrations, metoprolol also inhibits beta2-adrenoreceptors, chiefly located in the bronchial and vascular musculature.

Metoprolol has no intrinsic sympathomimetic activity, and membrane-stabilizing activity is detectable only at plasma concentrations much greater than required for beta-blockade. Animal and human experiments indicate that metoprolol slows the sinus rate and decreases AV nodal conduction.

The relative beta1-selectivity of metoprolol has been confirmed by the following: (1) In normal subjects, metoprolol is unable to reverse the beta2-mediated vasodilating effects of epinephrine. This contrasts with the effect of nonselective beta-blockers, which completely reverse the vasodilating effects of epinephrine. (2) In asthmatic patients, metoprolol reduces FEV1 and FVC significantly less than a nonselective beta-blocker, propranolol, at equivalent beta1-receptor blocking doses.

Hypertension: The mechanism of the antihypertensive effects of beta-blocking agents has not been elucidated. However, several possible mechanisms have been proposed: (1) competitive antagonism of catecholamines at peripheral (especially cardiac) adrenergic neuron sites, leading to decreased cardiac output; (2) a central effect leading to reduced sympathetic outflow to the periphery; and (3) suppression of renin activity.

Angina Pectoris: By blocking catecholamine-induced increases in heart rate, in velocity and extent of myocardial contraction, and in blood pressure, metoprolol reduces the oxygen requirements of the heart at any given level of effort, thus making it useful in the long-term management of angina pectoris.

Heart Failure: The precise mechanism for the beneficial effects of beta-blockers in heart failure has not been elucidated.

12.2 Pharmacodynamics

Clinical pharmacology studies have confirmed the beta-blocking activity of metoprolol in man, as shown by (1) reduction in heart rate and cardiac output at rest and upon exercise, (2) reduction of systolic blood pressure upon exercise, (3) inhibition of isoproterenol-induced tachycardia, and (4) reduction of reflex orthostatic tachycardia.

The relationship between plasma metoprolol levels and reduction in exercise heart rate is independent of the pharmaceutical formulation. Beta1-blocking effects in the range of 30-80% of the maximal effect (approximately 8 to 23% reduction in exercise heart rate) correspond to metoprolol plasma concentrations from 30 to 540 nmol/L. The relative beta1-selectivity of metoprolol diminishes and blockade of beta2-adrenoceptors increases at plasma concentration above 300 nmol/L.

Significant beta-blocking effect (as measured by reduction of exercise heart rate) occurs within 1 hour after oral administration, and its duration is dose-related. For example, a 50% reduction of the maximum effect after single oral doses of 20, 50, and 100 mg occurred at 3.3, 5.0, and 6.4 hours, respectively, in normal subjects. After repeated oral dosages of 100 mg twice daily, a significant reduction in exercise systolic blood pressure was evident at 12 hours. When the drug was infused over a 10-minute period, in normal volunteers, maximum beta-blockade was achieved at approximately 20 minutes. Equivalent maximal beta-blocking effect is achieved with oral and intravenous doses in the ratio of approximately 2.5:1.

There is a linear relationship between the log of plasma levels and reduction of exercise heart rate. However, antihypertensive activity does not appear to be related to plasma levels. Because of variable plasma levels attained with a given dose and lack of a consistent relationship of antihypertensive activity to dose, selection of proper dosage requires individual titration.

In several studies of patients with acute myocardial infarction, intravenous followed by oral administration of Lopressor caused a reduction in heart rate, systolic blood pressure and cardiac output. Stroke volume, diastolic blood pressure and pulmonary artery end diastolic pressure remained unchanged.

12.3 Pharmacokinetics

Absorption: The estimated oral bioavailability of immediate release metoprolol is about 50% because of pre-systemic metabolism which is saturable leading to non-proportionate increase in the exposure with increased dose.

Distribution: Metoprolol is extensively distributed with a reported volume of distribution of 3.2 to 5.6 L/kg. About 10% of metoprolol in plasma is bound to serum albumin. Metoprolol is known to cross the placenta and is found in breast milk. Metoprolol is also known to cross the blood brain barrier following oral administration and CSF concentrations close to that observed in plasma have been reported. Metoprolol is not a significant P-glycoprotein substrate.

Elimination: Elimination of Lopressor is mainly by biotransformation in the liver. The mean elimination half-life of metoprolol is 3 to 4 hours; in poor CYP2D6 metabolizers the half-life may be 7 to 9 hours.

Metabolism: Lopressor is primarily metabolized by CYP2D6. Metoprolol is a racemic mixture of R- and S- enantiomers, and when administered orally, it exhibits stereoselective metabolism that is dependent on oxidation phenotype. CYP2D6 is absent (poor metabolizers) in about 8% of Caucasians and about 2% of most other populations. Poor CYP2D6 metabolizers exhibit several-fold higher plasma concentrations of Lopressor than extensive metabolizers with normal CYP2D6 activity thereby decreasing Lopressor’s cardioselectivity.

Excretion

Approximately 95% of the dose can be recovered in urine. In most subjects (extensive metabolizers), less than 5% of an oral dose and less than 10% of an intravenous dose are excreted as unchanged drug in the urine. In poor metabolizers, up to 30% or 40% of oral or intravenous doses, respectively, may be excreted unchanged; the rest is excreted by the kidneys as metabolites that appear to have no beta-blocking activity. The renal clearance of the stereo-isomers does not exhibit stereo-selectivity in renal excretion.

Specific populations

Geriatric patients: The geriatric population may show slightly higher plasma concentrations of metoprolol as a combined result of a decreased metabolism of the drug in elderly population and a decreased hepatic blood flow. However, this increase is not clinically significant or therapeutically relevant.

Renal impairment: The systemic availability and half-life of Lopressor in patients with renal failure do not differ to a clinically significant degree from those in normal subjects.

Hepatic Impairment: Since the drug is primarily eliminated by hepatic metabolism, hepatic impairment may impact the pharmacokinetics of metoprolol.

Drug Interactions

Metoprolol is metabolized predominantly by CYP2D6. In healthy subjects with CYP2D6 extensive metabolizer phenotype, coadministration of quinidine 100 mg, a potent CYP2D6 inhibitor, and immediate-release metoprolol 200 mg tripled the concentration of S-metoprolol and doubled the metoprolol elimination half-life. In four patients with cardiovascular disease, coadministration of propafenone 150 mg t.i.d. with immediate-release metoprolol 50 mg t.i.d. increased the steady-state metoprolol concentration 2- to 5-fold compared to metoprolol alone. Extensive metabolizers who concomitantly use CYP2D6 inhibiting drugs will have increased (several-fold) metoprolol blood levels, decreasing metoprolol's cardioselectivity [see Drug Interactions (7.2)].

12.5 Pharmacogenomics

CYP2D6 is absent in about 8% of Caucasians (poor metabolizers) and about 2% of most other populations. CYP2D6 can be inhibited by several drugs. Poor metabolizers of CYP2D6 will have increased (several-fold) metoprolol blood levels, decreasing metoprolol's cardioselectivity.

13 NONCLINICAL TOXICOLOGY

13.1 Carcinogenesis, Mutagenesis, Impairment of Fertility

Long-term studies in animals have been conducted to evaluate the carcinogenic potential of metoprolol tartrate. In 2-year studies in rats at three oral dosage levels of up to 800 mg/kg/day (19 times, on a mg/m^2 basis, the daily dose of 400 mg for a 60-kg patient), there was no increase in the development of spontaneously occurring benign or malignant neoplasms of any type. The only histologic changes that appeared to be drug related were an increased incidence of generally mild focal accumulation of foamy macrophages in pulmonary alveoli and a slight increase in biliary hyperplasia. In a 21-month study in Swiss albino mice at three oral dosage levels of up to 750 mg/kg/day (9 times, on a mg/m^2 basis, the daily dose of 400 mg for a 60-kg patient), benign lung tumors (small adenomas) occurred more frequently in female mice receiving the highest dose than in untreated control animals. There was no increase in malignant or total (benign plus malignant) lung tumors, nor in the overall incidence of tumors or malignant tumors. This 21-month study was repeated in CD-1 mice, and no statistically or biologically significant differences were observed between treated and control mice of either sex for any type of tumor.

All genotoxicity tests performed on metoprolol tartrate (a dominant lethal study in mice, chromosome studies in somatic cells, a Salmonella/mammalian-microsome mutagenicity test, and a nucleus anomaly test in somatic interphase nuclei) and metoprolol succinate (a Salmonella/mammalian-microsome mutagenicity test) were negative.

No evidence of impaired fertility due to metoprolol tartrate was observed in a study performed in rats at doses up to 55.5 times, on a mg/m^2 basis, the daily dose of 450 mg in a 60-kg patient.

14 CLINICAL STUDIES

14.1 Hypertension

In controlled clinical studies, Lopressor has been shown to be an effective antihypertensive agent when used alone or as concomitant therapy with thiazide-type diuretics, at dosages of 100 mg to 450 mg daily. In controlled, comparative, clinical studies, Lopressor has been shown to be as effective an antihypertensive agent as propranolol, methyldopa, and thiazide-type diuretics, to be equally effective in supine and standing positions.

14.2 Angina Pectoris

In controlled clinical trials, Lopressor, administered two or four times daily, has been shown to be an effective antianginal agent, reducing the number of angina attacks and increasing exercise tolerance. The dosage used in these studies ranged from 100 mg to 400 mg daily. A controlled, comparative, clinical trial showed that Lopressor was indistinguishable from propranolol in the treatment of angina pectoris.

14.3 Myocardial Infarction

In a large (1395 patients randomized), double-blind, placebo-controlled clinical study, Lopressor was shown to reduce 3-month mortality by 36% in patients with suspected or definite myocardial infarction.

Patients were randomized and treated as soon as possible after their arrival in the hospital, once their clinical condition had stabilized and their hemodynamic status had been carefully evaluated. Subjects were ineligible if they had hypotension, bradycardia, peripheral signs of shock, and/or more than minimal basal rales as signs of congestive heart failure. Initial treatment consisted of intravenous followed by oral administration of Lopressor or placebo, given in a coronary care or comparable unit. Oral maintenance therapy with Lopressor or placebo was then continued for 3 months. After this double-blind period, all patients were given Lopressor and followed up to 1 year.

The median delay from the onset of symptoms to the initiation of therapy was 8 hours in both the Lopressor- and placebo-treatment groups. Among patients treated with Lopressor, there were comparable reductions in 3-month mortality for those treated early (≤ 8 hours) and those in whom treatment was started later. Significant reductions in the incidence of ventricular fibrillation and in chest pain following initial intravenous therapy were also observed with Lopressor and were independent of the interval between onset of symptoms and initiation of therapy.

In this study, patients treated with metoprolol received the drug both very early (intra-venously) and during a subsequent 3-month period, while placebo patients received no beta-blocker treatment for this period. The study thus was able to show a benefit from the overall metoprolol regimen but cannot separate the benefit of very early intravenous treatment from the benefit of later beta-blocker therapy. Nonetheless, because the overall regimen showed a clear beneficial effect on survival without evidence of an early adverse effect on survival, one acceptable dosage regimen is the precise regimen used in the trial. Because the specific benefit of very early treatment remains to be defined however, it is also reasonable to administer the drug orally to patients at a later time as is recommended for certain other beta-blockers.

16 HOW SUPPLIED/STORAGE AND HANDLING

Lopressor (metoprolol tartrate) tablets

Tablets 50 mg – capsule-shaped, biconvex, pink, scored (imprinted LOPRESSOR on one side and 458 twice on the scored side)

Bottles of 100………………………………………….………NDC 30698-458-01

Tablets 100 mg – capsule-shaped, biconvex, light blue, scored (imprinted LOPRESSOR on one side and 459 twice on the scored side)

Bottles of 100…………………………………………………. NDC 30698-459-01

Storage:
Store at 77°F (25°C); excursions permitted to 59° to 86°F (15° to 30°C) [See USP Controlled Room Temperature]. Protect from moisture and heat.

Dispense in a tight, light-resistant container (USP).

17 PATIENT COUNSELING INFORMATION

Advise patients to take LOPRESSOR regularly and continuously, as directed, preferably with or immediately following meals. If a dose is missed, the patient should take only the next scheduled dose (without doubling it). Patients should not interrupt or discontinue LOPRESSOR without consulting the physician.

Advise patients (1) to avoid operating automobiles and machinery or engaging in other tasks requiring alertness until the patient’s response to therapy with LOPRESSOR has been determined; (2) to contact the physician if any difficulty in breathing occurs; (3) to inform the physician or dentist before any type of surgery that he or she is taking LOPRESSOR.

Inform patients or caregivers that there is a risk of hypoglycemia when LOPRESSOR is given to patients who are fasting or who are vomiting. Monitor for symptoms of hypoglycemia.

Manufactured for and Distributed by:
Validus Pharmaceuticals LLC
Parsippany, NJ 07054
info@validuspharma.com
www.validuspharma.com
1-866-982-5438

Product of Spain

© 2023 Validus Pharmaceuticals LLC

60025-06

PACKAGE LABEL

PRINCIPAL DISPLAY PANEL

NDC 30698-458-01
Lopressor
(metoprolol tartrate USP) Tablets
50 mg
100 Tablets
Rx Only

PACKAGE LABEL

PRINCIPAL DISPLAY PANEL

NDC 30698-459-01
Lopressor
(metoprolol tartrate USP) Tablets
100 mg
100 Tablets
Rx Only